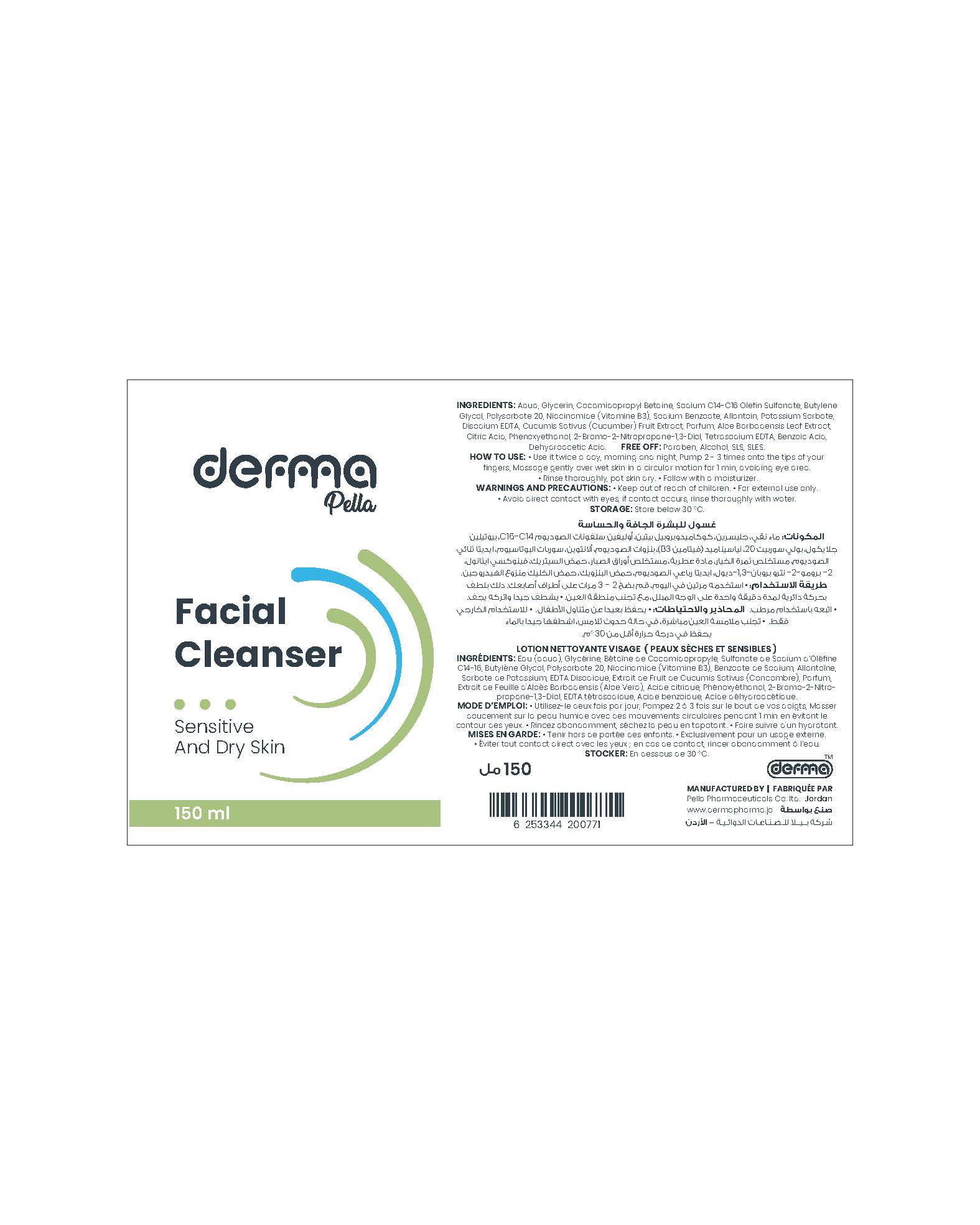 DRUG LABEL: Derma Pella Cleanser for Sensitive and Dry Skin
NDC: 82160-771 | Form: SOLUTION
Manufacturer: Pella Pharmaceuticals Co. Ltd
Category: otc | Type: HUMAN OTC DRUG LABEL
Date: 20241231

ACTIVE INGREDIENTS: NIACINAMIDE 5 mg/1 mL
INACTIVE INGREDIENTS: GLYCERIN; COCAMIDOPROPYL BETAINE; BUTYLENE GLYCOL; EDETATE DISODIUM ANHYDROUS; ALOE VERA LEAF; CITRIC ACID MONOHYDRATE; SODIUM BENZOATE; PHENOXYETHANOL; ALLANTOIN; DEHYDROACETIC ACID; WATER; SODIUM C14-16 OLEFIN SULFONATE; BRONOPOL; EDETATE SODIUM; POLYSORBATE 20; POTASSIUM SORBATE; CUCUMBER; BENZOIC ACID

Cleanser for sensitive skin

Form and Presentation

Solution: Plastic Bottle, 150 ml

Active Ingredient

Niacinamide (Vitamin B3)

Inactive Ingredients

Aqua, Glycerin, Cocamidopropyl Betain, Sodium C14-16 Olefin Sulfonate, Butylene Glycol, Polysorbate 20, Sodium Benzoate, Allantoin, Potassium Sorbate, Disodium EDTA, Cucumis Sativus (Cucumber) Fruit Extract, Parfum, Aloe Barbadensis (Aloe Vera) Leaf Extract, Citric Acid, Phenoxyethanol, 2-Bromo-2-Nitropropane-1,3-Diol, Tetrasodium EDTA, Benzoic Acid, Dehydroacetic Acid.

Purpose

Facial Cleanser for Sensitive and Dry Skin

Properties

A refreshing cleanser for sensitive and dry skin. It cleanses gently without a harsh drying effect, leaving your skin feeling refreshed. A combination of Aloe Vera, Cucumber Extracts, Vitamin B3 and Allantoin make it perfect for daily use.

Aloe Vera Extract soothes irritated skin, increase skin hydration, fights bacteria and shields skin from pollutants and free radicals.

Cucumber Extract is a good skin rejuvenator, cools, refreshes tones and firms skin for clean and fresh feeling and improving skin elasticity.

Niacinamide (Vitamin B3) helps soothe and balance the appearance of skin tone.

Allantoin which is an effective moisturizing ingredient used for it is gentle and non-irritating qualities.

Paraben free, Alcohol free, SLS free, SLES free.

Indications

A mild facial cleanser for sensitive and dry skin.

Precautions

Keep out of reach of children

Warnings

- For external use only.
- Avoid direct contact with eyes, if contact occurs, rinse thoroughly with water.

Contraindications

Hypersensitivity to any of the components.

Side Effects

It is well tolerated product there is no known side effect.

Dosage and Administration

- Use it twice a day, morning and night.
- Pump 2 - 3 times onto the tips of your fingers.
- Massage gently over wet skin in a circular motion for 1 min, avoiding eye area.
- Rinse thoroughly, pat skin dry.
- Follow with a moisturizer.

Storage Conditions

Store below 30◦C